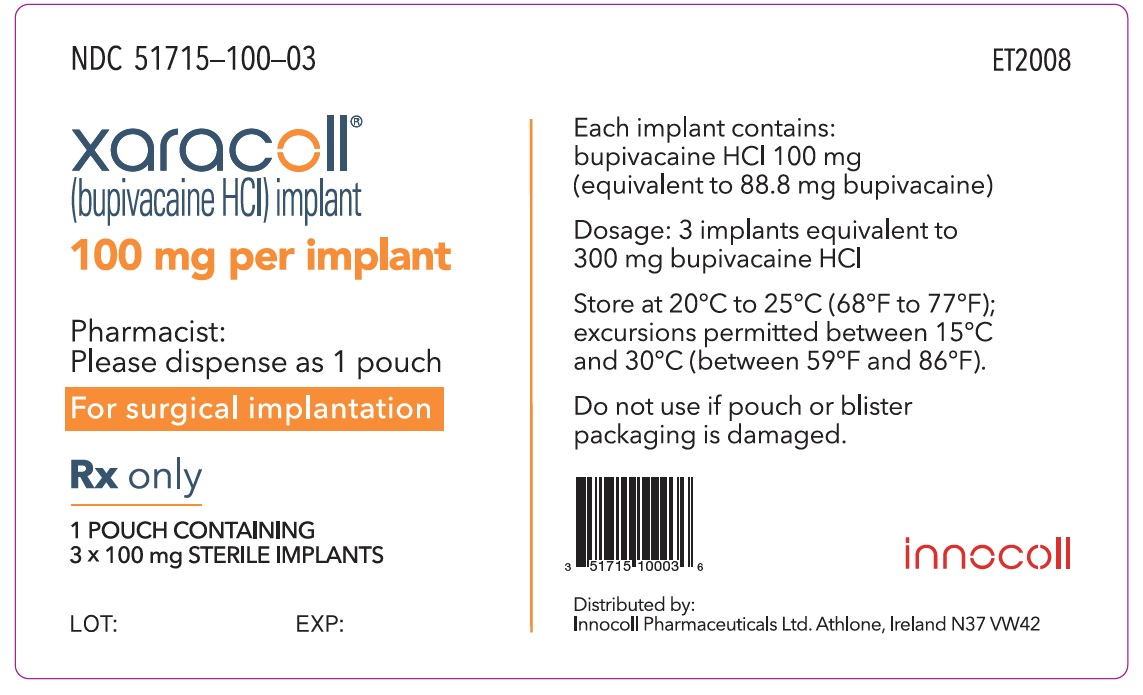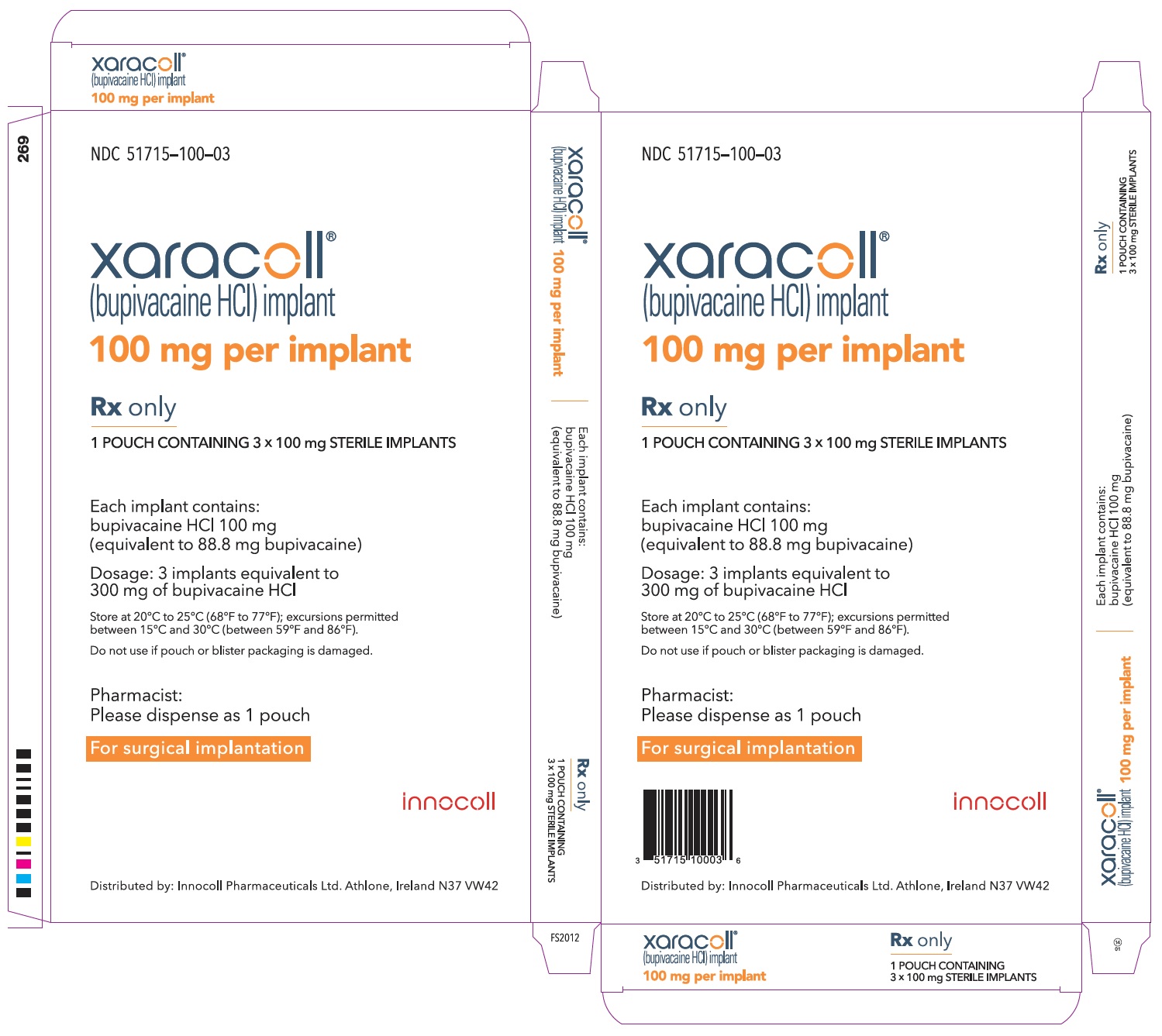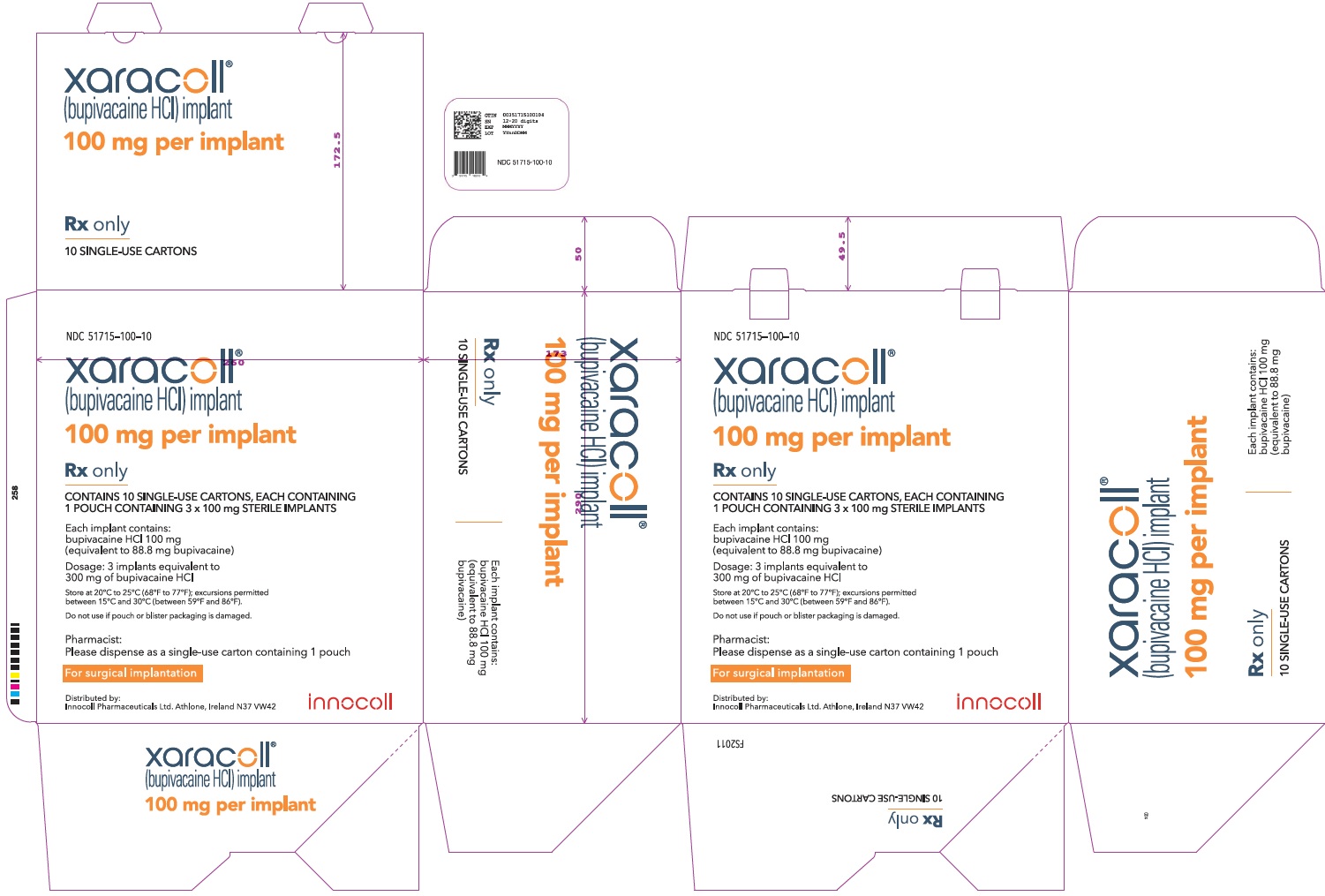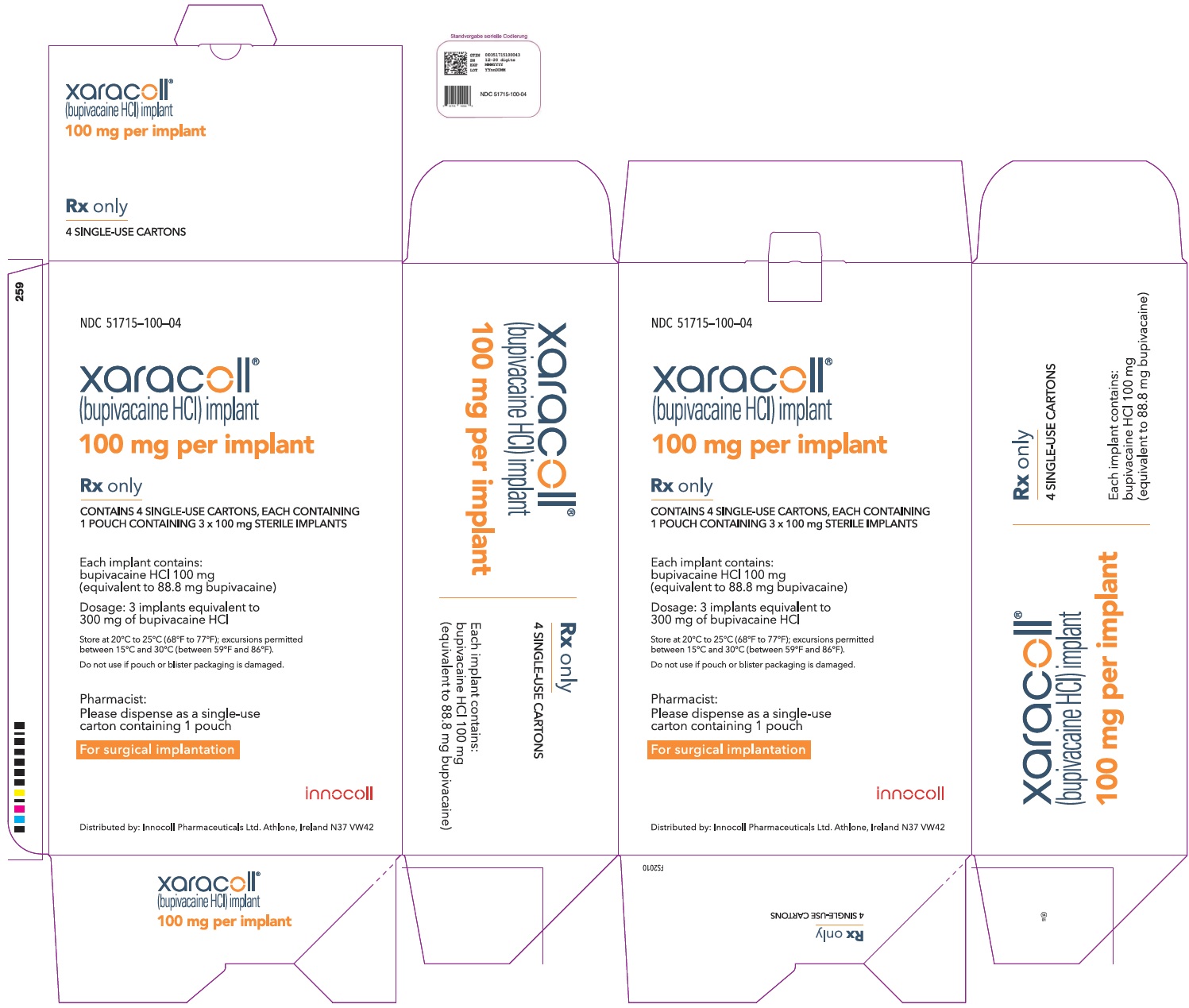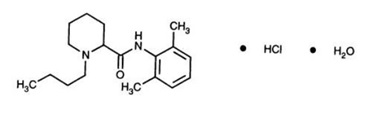 DRUG LABEL: XARACOLL
NDC: 51715-100 | Form: IMPLANT
Manufacturer: INNOCOLL PHARMACEUTICALS
Category: prescription | Type: HUMAN PRESCRIPTION DRUG LABEL
Date: 20200908

ACTIVE INGREDIENTS: BUPIVACAINE 100 mg/1 1

HIGHLIGHTS OF PRESCRIBING INFORMATION

These highlights do not include all the information needed to use XARACOLL® safely and effectively. See full prescribing information for XARACOLL.
XARACOLL® (bupivacaine hydrochloride) implant
Initial U.S. Approval: 1972

1. INDICATIONS AND USAGE

XARACOLL contains an amide local anesthetic and is indicated in adults for placement into the surgical site to produce postsurgical analgesia for up to 24 hours following open inguinal hernia repair (1).

Limitations of Use
Safety and effectiveness have not been established in other surgical procedures, including orthopedic and boney procedures (5.5).

2. DOSAGE AND ADMINISTRATION

- XARACOLL is intended for single-dose administration. The recommended dose is 300 mg bupivacaine HCl (three XARACOLL implants, each containing 100 mg bupivacaine HCl) (2.2).
- Each XARACOLL implant should be cut in half using aseptic technique prior to placing the dry implants into the surgical site. Place three halves below the site of mesh placement and three halves just below the skin closure. (2.3).

3. DOSAGE FORMS AND STRENGTHS

100 mg per implant (3)

4. CONTRAINDICATIONS

• Known hypersensitivity to bupivacaine or to any local anesthetic agent of the amide-type or to other components of XARACOLL (4).
• Obstetrical paracervical block anesthesia. The use of bupivacaine in this technique has resulted in fetal bradycardia and death (4).

5. WARNINGS AND PRECAUTIONS

- Dose-Related Toxicity: Monitor cardiovascular and respiratory vital signs and patient’s state of consciousness after placement of XARACOLL. (5.1)
- Methemoglobinemia: Cases of methemoglobinemia have been reported in association with local anesthetic use. See full prescribing information for more detail on managing these risks (5.2).

6. ADVERSE REACTIONS

Most common adverse reactions in clinical trials (incidence ≥2% and higher than placebo) included incision site swelling, dysgeusia, headache, tremor, vision blurred, seroma, scrotal swelling, pyrexia, hypoesthesia oral, and post procedural discharge. (6.1).

To report SUSPECTED ADVERSE REACTIONS, contact Innocoll at 1-833-606-1421 or FDA at 1-800-FDA-1088 or www.fda.gov/medwatch.

7. DRUG INTERACTIONS

Local Anesthetics: The toxic effects of local anesthetics are additive. Avoid additional local anesthetic administration within 96 hours following XARACOLL implantation. If additional local anesthetic administration with XARACOLL cannot be avoided, monitor patients for neurologic and cardiovascular effects related to local anesthetic systemic toxicity (7.1).

8. USE IN SPECIFIC POPULATIONS

- Pregnancy: based on animal data, may cause fetal harm (8.1).
- Moderate to Severe Hepatic Impairment: Consider increased monitoring for bupivacaine systemic toxicity (8.6).

FULL PRESCRIBING INFORMATION

1. INDICATIONS AND USAGE

XARACOLL is indicated in adults for placement into the surgical site to produce postsurgical analgesia for up to 24 hours following open inguinal hernia repair.

Limitations of Use

Safety and effectiveness have not been established in other surgical procedures, including orthopedic and boney procedures [see Warnings and Precautions (5.5)].

2. DOSAGE AND ADMINISTRATION

2.1 Important Dosage and Administration Information

- XARACOLL is to be administered by or under the supervision of experienced clinicians who are well versed in the diagnosis and management of dose-related toxicity and other acute emergencies which might arise from bupivacaine exposure.
- The toxic effects of local anesthetics are additive. Avoid additional local anesthetic administration within 96 hours following XARACOLL implantation. If additional local anesthetic administration with XARACOLL cannot be avoided based on clinical need, monitor patients for neurologic and cardiovascular effects related to local anesthetic systemic toxicity [see Warnings and Precautions (5.1), Drug Interactions (7), Overdosage (10)].
- Use XARACOLL only if the following are immediately available: oxygen, other resuscitative drugs, cardiopulmonary resuscitative equipment, and the personnel resources needed for proper management of toxic reactions and related emergencies [see Warnings and Precautions (5.1), Adverse Reactions (6), Overdosage (10)].
- XARACOLL is supplied as a sterile product that should be handled using aseptic technique. XARACOLL is designed as a ready-to-use product and requires no preparation other than cutting the individual implants as needed to accommodate the surgical space.
- Each single-dose package (pouch) of XARACOLL contains three implants comprising the total dose of 300 mg bupivacaine HCl. Inspect the outer pouch and inner blister packaging prior to use. Do not use XARACOLL if the packaging has been compromised.
- XARACOLL is white to off-white in color, has uniform thickness, and is approximately 5 cm × 5 cm × 0.5 cm in size. Do not use XARACOLL if it appears discolored, contains foreign particulates, or is collapsed, compressed, or misshapen.
- Avoid excessive handling and compression of XARACOLL.
- Avoid contact of XARACOLL with liquids prior to placement. Place the XARACOLL implant into the surgical site dry. Pre-moistening may result in premature release of bupivacaine from XARACOLL.

2.2 Recommended Dose

- XARACOLL is intended for single-dose administration. The recommended dose of XARACOLL is 300 mg (3 x 100 mg implants).
- Doses of XARACOLL above 300 mg (3 x 100 mg implants) per patient have not been studied in clinical trials.

2.3 Placement Instructions

- Both the outer pouch and the inner blister packaging containing the individual implants are designed to be peeled open. Aseptically peel open the outer pouch, then remove and aseptically peel open the three inner blister packages containing XARACOLL. To avoid cutting the implants prior to placement, do not open the blister packaging using scissors or a scalpel.
- Carefully remove XARACOLL from the inner blister packages and inspect each implant prior to use.
- Using aseptic technique, cut each XARACOLL implant in half prior to placement into the surgical site. Place three halves below the site of mesh placement and three halves just below the skin closure.
- XARACOLL may become difficult to move once placed in the surgical site and moistened. Use care when moving XARACOLL after placement.

2.4 Compatibility Considerations

Administration of additional local anesthetics, including bupivacaine HCl, into the surgical site with XARACOLL has not been studied.

Studies conducted with XARACOLL demonstrated that commonly used surgical materials (nonabsorbable surgical suture, delayed absorbable surgical suture, and surgical mesh) are not affected by the presence of XARACOLL.

When a topical antiseptic such as povidone iodine (e.g., Betadine®) is applied, allow the surgical site to dry before XARACOLL is administered.

3. DOSAGE FORMS AND STRENGTHS

XARACOLL (bupivacaine HCl) implant

- 100 mg bupivacaine HCl (equivalent to 88.8 mg bupivacaine) per implant; each implant is white to off-white in color and is approximately 5 cm × 5 cm × 0.5 cm in size

4. CONTRAINDICATIONS

XARACOLL is contraindicated in:

- patients with a known hypersensitivity to any local anesthetic agent of the amide-type or to any of the other components of XARACOLL.
- patients undergoing obstetrical paracervical block anesthesia. The use of bupivacaine in this technique has resulted in fetal bradycardia and death.

5. WARNINGS AND PRECAUTIONS

5.1 Dose-related Toxicity

The safety and effectiveness of local anesthetics depend on proper dosage, correct technique, adequate precautions, and readiness for emergencies. The toxic effects of local anesthetics are additive. Avoid additional local anesthetic administration within 96 hours following XARACOLL implantation. If additional local anesthetic administration with XARACOLL cannot be avoided based on clinical need, monitor patients for neurologic and cardiovascular effects related to local anesthetic systemic toxicity. Careful and constant monitoring of cardiovascular and respiratory (adequacy of ventilation) vital signs and the patient’s state of consciousness should be performed after administration of XARACOLL.

Possible early warning signs of central nervous system (CNS) toxicity are restlessness, anxiety, incoherent speech, lightheadedness, numbness and tingling of the mouth and lips, metallic taste, tinnitus, dizziness, blurred vision, tremors, twitching, CNS depression, or drowsiness. Delay in proper management of dose-related toxicity, underventilation from any cause, and/or altered sensitivity may lead to the development of acidosis, cardiac arrest, and, possibly, death. Consider surgical removal of XARACOLL depending on the clinical situation.

5.2 Methemoglobinemia

Cases of methemoglobinemia have been reported in association with local anesthetic use. Although all patients are at risk for methemoglobinemia, patients with glucose-6-phosphate dehydrogenase deficiency, congenital or idiopathic methemoglobinemia, cardiac or pulmonary compromise, infants under 6 months of age, and concurrent exposure to oxidizing agents or their metabolites are more susceptible to developing clinical manifestations of the condition. If local anesthetics must be used in these patients, close monitoring for symptoms and signs of methemoglobinemia is recommended.

Signs of methemoglobinemia may occur immediately or may be delayed some hours after exposure, and are characterized by a cyanotic skin discoloration and/or abnormal coloration of the blood. Methemoglobin levels may continue to rise; therefore, immediate treatment is required to avert more serious CNS and cardiovascular adverse effects, including seizures, coma, arrhythmias, and death. Consider removal of XARACOLL and discontinue any other oxidizing agents. Depending on the severity of the signs and symptoms, patients may respond to supportive care, i.e., oxygen therapy, hydration. A more severe clinical presentation may require treatment with methylene blue, exchange transfusion, or hyperbaric oxygen.

5.3 Risk of Toxicity in Patients with Hepatic Impairment

Because amide local anesthetics such as bupivacaine are metabolized by the liver, consider increased monitoring for bupivacaine systemic toxicity in patients with moderate to severe hepatic impairment who are treated with XARACOLL [see Use in Specific Populations (8.6)].

5.4 Risk of Use in Patients with Impaired Cardiovascular Function

Patients with impaired cardiovascular function (e.g., hypotension, heart block) may be less able to compensate for functional changes associated with the prolongation of AV conduction produced by XARACOLL. Monitor patients closely for blood pressure, heart rate, and ECG changes.

5.5 Risk of Delayed Bone Healing with Unapproved Use

The safety and effectiveness of XARACOLL in surgical procedures other than open inguinal hernia repair have not been established, and XARACOLL is not approved for use in these other surgical procedures (e.g., orthopedic procedures). A study evaluating the effects of bupivacaine HCl implant in rats following an osteotomy procedure demonstrated inhibition of bone healing [see Nonclinical Toxicology (13.2)].

6. ADVERSE REACTIONS

The following clinically significant adverse reactions have been reported and described in the Warnings section in the labeling:

- Dose-Related Toxicity [see Warnings and Precautions (5.1)]
- Methemoglobinemia [see Warnings and Precautions (5.2)]

6.1 Clinical Trial Experience

Because clinical studies are conducted under widely varying conditions, adverse reaction rates observed in the clinical trials of a drug cannot be directly compared to rates in the clinical studies of another drug and may not reflect the rates observed in practice.

The safety of XARACOLL was evaluated in 11 clinical studies, including two Phase 3 double-blind, placebo implant-controlled studies in patients undergoing open, unilateral inguinal hernia repair. Overall, 612 patients were treated with a single dose of XARACOLL, total dose ranged from 100 mg to 300 mg bupivacaine HCl. Patients treated with XARACOLL ranged in age from 18 to 85 years (median age 51 years), with 88% male, 88% White, 9% African-American, and 3% all other races.

Across the XARACOLL drug development program, which included evaluations in various surgery models, there was one patient death reported in the placebo implant treatment group, and 16 patients who experienced one or more serious adverse events; 11 patients in the XARACOLL treatment group and 5 patients in the placebo implant or comparator treatment groups. Serious adverse reactions reported in the XARACOLL treatment group included wound infection and seroma. There was a single patient who experienced signs and symptoms consistent with local anesthetic systemic toxicity (LAST) approximately four hours after administration of an early formulation of the bupivacaine collagen implant 150 mg during bladder sling surgery. LAST treatment included administration of lipid emulsion and surgical removal of the XARACOLL implants.

The most common adverse reactions (incidence greater than or equal to 2% and higher than placebo implant) following XARACOLL administration were dysgeusia, headache, scrotal swelling, tremor, pyrexia, vision blurred, and seroma. Common incision site adverse reactions (incidence greater than or equal to 2% and higher in either the XARACOLL or placebo implant groups compared to non-implant comparator treatment groups) were swelling pain, other complication, post-procedural discharge, erythema, dehiscence, and inflammation.

Adverse Reactions Reported in Phase 3 Placebo-controlled Trials

There were 619 patients who underwent open inguinal hernia repair in the two Phase 3 studies. Patients received general anesthesia intra-operatively, and a standard acetaminophen regimen, in addition to intravenous and oral morphine as needed, post-operatively. The most common adverse reactions (incidence greater than or equal to 2% and higher than placebo implants) following XARACOLL administration were incision site swelling, dysgeusia, headache, tremor, vision blurred, seroma, scrotal swelling, pyrexia, hypoesthesia oral, and post procedural discharge shown in Table 1.

Table 1: Adverse Reactions (ARs) with Incidence Greater Than or Equal to 2% and Greater Than Placebo Reported in the Phase 3 Placebo-controlled Studies
 | XARACOLL 300 mg N=411 n (%) | Placebo [Placebo consisted of three collagen implants.] N=208 n (%)
Subjects Reporting Treatment Emergent Adverse Events | 256 (62.3%) | 143 (68.8%)
Injury, Poisoning and Procedural Complications
Incision Site Swelling | 60 (14.6%) | 30 (14.4%)
Post Procedural Discharge | 20 (4.9%) | 10 (4.8%)
Seroma | 12 (2.9%) | 5 (2.4%)
Nervous System Disorders
Dysgeusia | 31 (7.5%) | 13 (6.3%)
Headache | 17 (4.1%) | 1 (0.5%)
Tremor | 15 (3.6%) | 6 (2.9%)
Gastrointestinal Disorders
Hypoaesthesia Oral | 9 (2.2%) | 4 (1.9%)
Reproductive System and Breast Disorders
Scrotal Swelling | 12 (2.9%) | 2 (1.0%)
General Disorders and Administration Site Conditions
Pyrexia | 10 (2.4%) | 1 (0.5%)
Eye Disorders
Vision Blurred | 15 (3.6%) | 6 (2.9%)

6.2 Postmarketing Experience

The following adverse reactions from voluntary reports have been reported with various formulations of bupivacaine, administered via different routes and for different indications. Because many of these reactions were reported voluntarily from a population of uncertain size, it is not always possible to reliably estimate their frequency or establish a causal relationship to drug exposure.

Adverse reactions to bupivacaine are characteristic of those associated with other amide-type local anesthetics. A major cause of adverse reactions to this group of drugs is excessive plasma levels, which may be due to overdosage, unintentional intravascular injection, or slow metabolic degradation.

The most commonly encountered acute adverse reactions that demand immediate counter-measures were related to the CNS and the cardiovascular system. These adverse reactions were generally dose-related and due to high plasma levels, which may have resulted from overdosage, rapid absorption from the injection site, diminished tolerance, or from unintentional intravascular injection of the local anesthetic solution.

Nervous System Disorders: Adverse reactions were characterized by excitation and/or depression of the central nervous system and included restlessness, anxiety, dizziness, tinnitus, blurred vision, tremors, convulsions, drowsiness, unconsciousness, respiratory arrest, nausea, vomiting, chills, pupillary constriction.

Neurological effects following routes of administration other than epidural or caudal have included persistent anesthesia, paresthesia, weakness, and paralysis, all with slow, incomplete, or no recovery.

The incidence of adverse neurologic reactions associated with the use of local anesthetics may be related to the total dose of local anesthetic administered and are also dependent upon the particular drug used, the route of administration, and the physical status of the patient.

Cardiac Disorders: High doses have led to high plasma levels and related depression of the myocardium, decreased cardiac output, heart block, hypotension, bradycardia, ventricular arrhythmias, including ventricular tachycardia and ventricular fibrillation, and cardiac arrest.

Immune System Disorders: Allergic-type reactions have occurred as a result of sensitivity to bupivacaine or to other formulation ingredients. These reactions were characterized by signs such as urticaria, pruritus, erythema, angioneurotic edema (including laryngeal edema), tachycardia, sneezing, nausea, vomiting, dizziness, syncope, excessive sweating, elevated temperature, and severe hypotension. Cross sensitivity among members of the amide-type local anesthetic group has been reported.

7. DRUG INTERACTIONS

7.1 Local Anesthetics

The toxic effects of local anesthetics are additive. Avoid additional local anesthetic administration within 96 hours following XARACOLL implantation. If additional local anesthetic administration with XARACOLL cannot be avoided based on clinical need, monitor patients for neurologic and cardiovascular effects related to local anesthetic systemic toxicity [see Dosage and Administration (2.1), Warnings and Precautions (5.1), Overdosage (10)].

7.2 Drugs Associated with Methemoglobinemia

Patients who are administered local anesthetics may be at increased risk of developing methemoglobinemia when concurrently exposed to the following drugs, which could include other local anesthetics:

Examples of Drugs Associated with Methemoglobinemia
Class | Examples
Nitrates/Nitrites | nitric oxide, nitroglycerin, nitroprusside, nitrous oxide
Local anesthetics | articaine, benzocaine, bupivacaine, lidocaine, mepivacaine, prilocaine, procaine, ropivacaine, tetracaine
Antineoplastic agents | cyclophosphamide, flutamide, hydroxyurea, ifosfamide, rasburicase
Antibiotics | dapsone, nitrofurantoin, para-aminosalicylic acid, sulfonamides
Antimalarials | chloroquine, primaquine
Anticonvulsants | phenobarbital, phenytoin, sodium valproate
Other drugs | acetaminophen, metoclopramide, quinine, sulfasalazine

8. USE IN SPECIFIC POPULATIONS

8.1 Pregnancy

Risk Summary

There are no studies conducted with XARACOLL in pregnant women to inform a drug-associated risk of adverse development outcomes. In animal studies, embryo-fetal lethality was noted when bupivacaine was administered subcutaneously to pregnant rabbits during organogenesis at clinically relevant doses. Decreased pup survival was observed in a rat pre- and post-natal developmental study (dosing from implantation through weaning) at a dose level comparable to the daily maximum recommended human dose (MRHD). Based on animal data, advise pregnant women of the potential risks to a fetus.

The estimated background risk of major birth defects and miscarriage for the indicated population is unknown. All pregnancies have a background risk of birth defect, loss, or other adverse outcomes. In the U.S. general population, the estimated background risk of major birth defects and miscarriage in clinically recognized pregnancies is 2-4% and 15-20%, respectively.

Clinical Considerations

Labor or Delivery

Local anesthetics rapidly cross the placenta [see Pharmacokinetics (12.3)]. The incidence and degree of toxicity depend upon the procedure performed, the type and amount of drug used, and the technique of drug administration. Adverse reactions in the parturient, fetus, and neonate involve alterations of the CNS, peripheral vascular tone, and cardiac function.

Data

Animal Data

Bupivacaine hydrochloride produced developmental toxicity when administered subcutaneously to pregnant rats and rabbits at clinically relevant doses.

Bupivacaine HCl was administered subcutaneously to rats at doses of 4.4, 13.3 and 40 mg/kg and to rabbits at doses of 1.3, 5.8 and 22.2 mg/kg during the period of organogenesis (implantation to closure of the hard palate). No embryo-fetal effects were observed in rats at up to 40 mg/kg, a dose that caused increased maternal lethality. This dose is approximately 1.3 times the daily maximum recommended human dose (MRHD) of 300 mg when calculated on a mg/m^2 body surface area (BSA) for a 60 kg woman. An increase in embryo-fetal deaths was observed in rabbits at the high dose (1.4 times the MHRD based on BSA) in the absence of maternal toxicity with the fetal No Observed Adverse Effect Level representing approximately 0.4 times the MRHD on a BSA basis.

In a rat pre- and post-natal development study (dosing from implantation through weaning) conducted at subcutaneous doses of 4.4, 13.3, and 40 mg/kg/day, decreased pup survival was observed at the high dose. The high dose is approximately 1.3 times the daily MRHD on a BSA basis.

8.2 Lactation

Risk Summary

Bupivacaine has been reported to be excreted in human milk suggesting that the nursing infant could be theoretically exposed to a dose of the drug. There is no available information on effects of the drug in the breastfed infant or effects of the drug on milk production. The developmental and health benefits of breastfeeding should be considered along with the mother’s clinical need for XARACOLL and any potential adverse effects on the breastfed infant from XARACOLL or from the underlying maternal condition.

8.4 Pediatric Use

Safety and effectiveness in pediatric patients have not been established.

8.5 Geriatric Use

Of the total number of patients in the Phase 3 XARACOLL studies (N=411), 60 patients were greater than or equal to 65 years of age and 14 patients were greater than or equal to 75 years of age. No overall differences in efficacy and safety were observed between these patients and younger patients. Clinical experience with XARACOLL has not identified differences in efficacy or safety between elderly and younger patients, but greater sensitivity of some older individuals cannot be ruled out.

In clinical studies of bupivacaine, differences in various pharmacokinetic parameters have been observed between elderly and younger patients. Bupivacaine is known to be substantially excreted by the kidney, and the risk of adverse reactions to this drug may be greater in patients with impaired renal function. Because elderly patients are more likely to have decreased renal function, it may be useful to monitor renal function. The effects of age (elderly versus younger) on the pharmacokinetics of XARACOLL have not been studied.

8.6 Hepatic Impairment

Amide-type local anesthetics, such as bupivacaine, are metabolized by the liver. Patients with severe hepatic disease, because of their inability to metabolize local anesthetics normally, are at a greater risk of developing toxic plasma concentrations and potentially local anesthetic systemic toxicity. Consider increased monitoring for local anesthetic systemic toxicity in subjects with moderate to severe hepatic disease [see Warnings and Precautions (5.3), Clinical Pharmacology (12.3)].

8.7 Renal Impairment

Bupivacaine is known to be substantially excreted by the kidney, and the risk of adverse reactions to this drug may be greater in patients with impaired renal function. Patients with severe renal disease, may be more susceptible to the potential toxicities of the amide-type local anesthetics. Consider increased monitoring for local anesthetic systemic toxicity in subjects with renal disease [see Clinical Pharmacology (12.3)].

10. OVERDOSAGE

Clinical Presentation

Acute emergencies from local anesthetics are generally related to high plasma concentrations encountered during therapeutic use of local anesthetics [see Warnings and Precautions (5.1), Adverse Reactions (6)].

If not treated immediately, convulsions with simultaneous hypoxia, hypercarbia, and acidosis plus myocardial depression from the direct effects of bupivacaine may result in cardiac arrhythmias, bradycardia, asystole, ventricular fibrillation, or cardiac arrest. Respiratory abnormalities, including apnea, may occur. If cardiac arrest occurs, successful outcome may require prolonged resuscitative efforts.

Management

The first step in the management of systemic toxic reactions consists of immediate attention to the establishment and maintenance of a patent airway and effective assisted or controlled ventilation with 100% oxygen with a delivery system capable of permitting immediate positive airway pressure by mask. Endotracheal intubation, using drugs and techniques familiar to the clinician, may be indicated after initial administration of oxygen by mask if difficulty is encountered in the maintenance of a patent airway, or if prolonged ventilatory support (assisted or controlled) is indicated.

If necessary, use drugs to manage the convulsions. A bolus intravenous dose of a benzodiazepine will counteract CNS stimulation related to XARACOLL. Immediately after the institution of ventilatory measures, evaluate the adequacy of the circulation. Supportive treatment of circulatory depression may require Advance Cardiac Life Support measures.

Consider surgical removal of XARACOLL depending on the clinical situation.

11. DESCRIPTION

XARACOLL contains bupivacaine, an amide local anesthetic, as the active pharmaceutical ingredient. Each XARACOLL collagen implant (5 cm × 5 cm × 0.5 cm) contains 100 mg bupivacaine HCl (equivalent to 88.8 mg bupivacaine) and 75 mg purified Type I collagen.

Each implant is individually packaged in sterile blister packaging. Three implants are packaged in a single-use sterile pouch, for a total of 300 mg bupivacaine HCl (equivalent to 266.4 mg bupivacaine) and 225 mg purified Type I collagen.

The resorbable and biodegradable collagen component of the product serves as an inert delivery system and releases bupivacaine through diffusion from the porous collagen implant, which dissolves over time.

11.1 Active Ingredient

Bupivacaine HCl is a 1-butyl-N-(2,6-dimethylphenyl)-2-piperidinecarboxamide hydrochloride monohydrate, white crystalline powder that is freely soluble in 95% ethanol, soluble in water, and slightly soluble in acetone. The molecular formula of bupivacaine is C18H28N2O and its molecular weight is 288.4. It has the following structural formula:

12. CLINICAL PHARMACOLOGY

12.1 Mechanism of Action

Bupivacaine blocks the generation and the conduction of nerve impulses, presumably by increasing the threshold for electrical excitation in the nerve, by slowing the propagation of the nerve impulse, and by reducing the rate of rise of the action potential. Clinically, the order of loss of nerve function is (1) pain, (2) temperature, (3) touch, (4) proprioception, and (5) skeletal muscle tone.

12.2 Pharmacodynamics

Systemic absorption of bupivacaine produces effects on the cardiovascular system and CNS. At blood concentrations achieved with normal therapeutic doses, changes in cardiac conduction, excitability, refractoriness, contractility, and peripheral vascular resistance are minimal. However, toxic blood concentrations depress cardiac conduction and excitability, which may lead to atrioventricular block, ventricular arrhythmias, and cardiac arrest, sometimes resulting in fatalities. In addition, myocardial contractility is depressed and peripheral vasodilation occurs, leading to decreased cardiac output and arterial blood pressure. These cardiovascular changes are more likely to occur after unintended intravascular injection of liquid formulations of bupivacaine.

Following systemic absorption, bupivacaine can produce CNS stimulation, CNS depression, or both. Apparent central stimulation is manifested as restlessness, tremors, and shivering progressing to convulsions, followed by depression and coma progressing ultimately to respiratory arrest. However, bupivacaine has a primary depressant effect on the medulla and on higher centers. The depressed stage may occur without a prior excited state.

12.3 Pharmacokinetics

Local placement of XARACOLL within the surgical site during open inguinal hernia repair resulted in detectable plasma levels of bupivacaine at the first measured time point (0.5 hours) and throughout the 96-hour observation period [see Warnings and Precautions (5.1)]. Systemic plasma levels of bupivacaine following application of XARACOLL do not correlate with local efficacy.

Absorption

The rate of systemic absorption of bupivacaine is dependent on the total dose administered, the route of administration, and the vascularity of the administration site.

Pharmacokinetic parameters for XARACOLL following placement in the surgical site during hernioplasty are presented in Table 2.

Table 2: Pharmacokinetic Parameters for Bupivacaine After Placement of XARACOLL in the Surgical Site During Open Inguinal Hernia Repair
Parameter | XARACOLL 300 mg N=34
Cmax (ng/mL) [Arithmetic mean (SD)] [minimum, maximum] | 663 (264) [274, 1230]
Tmax (hours) [Median (SD)] [minimum, maximum] | 3 [1.5, 24]
AUC0-last (h•ng/mL)* | 19493 (7564)
AUC0-∞ (h•ng/mL)* | 20368 (7912)
t1/2 (hours)* | 19 (6)

The highest individual bupivacaine plasma concentration observed in the XARACOLL clinical program was 1230 ng/mL, which occurred 2 hours after placement of the three XARACOLL 100 mg implants (total bupivacaine HCl dose 300 mg) in the surgical site of one patient.

Distribution

After bupivacaine is released from XARACOLL it is absorbed systemically. Local anesthetics including bupivacaine are distributed to some extent to all body tissues, with higher concentrations found in highly perfused organs such as the liver, lungs, heart, and brain.

Local anesthetics including bupivacaine appear to cross the placenta by passive diffusion. The rate and degree of diffusion is governed by (1) the degree of plasma protein binding, (2) the degree of ionization, and (3) the degree of lipid solubility. Fetal/maternal ratios of local anesthetics appear to be inversely related to the degree of plasma protein binding, because only the free, unbound drug is available for placental transfer. Bupivacaine with a high protein binding capacity (95%) has a low fetal/maternal ratio (0.2 to 0.4). The extent of placental transfer is also determined by the degree of ionization and lipid solubility of the drug. Lipid soluble, non-ionized drugs such as bupivacaine readily enter the fetal blood from the maternal circulation.

Elimination

Metabolism

Amide-type local anesthetics such as bupivacaine are metabolized primarily in the liver via conjugation with glucuronic acid. Pipecoloxylidine is the major metabolite of bupivacaine. The elimination of drug from tissue distribution depends largely upon the availability of binding sites in the circulation to carry it to the liver where it is metabolized.

Excretion

After bupivacaine has been released from XARACOLL and is absorbed systemically, bupivacaine excretion is expected to be the same as for other bupivacaine formulations.

The kidney is the main excretory organ for most local anesthetics and their metabolites. Only 6% of bupivacaine is excreted unchanged in the urine.

Specific Populations

Age

Various pharmacokinetic parameters of the local anesthetics such as bupivacaine can be significantly altered by the age of the patient [see Geriatric Use (8.5)].

Hepatic Impairment

Various pharmacokinetic parameters of the local anesthetics can be significantly altered by the presence of hepatic disease. Patients with hepatic disease, especially those with severe hepatic disease, may be more susceptible to the potential toxicities of the amide-type local anesthetics [see Use in Specific Populations (8.6)].

Renal Impairment

Various pharmacokinetic parameters of the local anesthetics can be significantly altered by the presence of renal disease, factors affecting urinary pH, and renal blood flow [see Warnings and Precautions (5.1), Use in Specific Populations (8.7), Geriatric Use (8.5)].

13. NONCLINICAL TOXICOLOGY

13.1 Carcinogenesis, Mutagenesis, Impairment of Fertility

Carcinogenesis

Long-term studies in animals to evaluate the carcinogenic potential of bupivacaine hydrochloride have not been conducted.

Mutagenesis

Bupivacaine was not mutagenic or clastogenic in a bacterial reverse mutation assay, an in vitro mammalian cell gene mutation test, and an in vivo mammalian erythrocyte micronucleus assay.

Impairment of Fertility

The effect of bupivacaine on fertility has not been determined.

13.2 Animal Toxicology and/or Pharmacology

Bupivacaine collage-matrix implants delayed bone healing in a rat osteotomy model compared to saline, bupivacaine, or placebo collagen implant alone. The clinical significance of these delays is not known.

14. CLINICAL STUDIES

The efficacy and safety of XARACOLL were evaluated in two randomized, multi-center, double-blind, placebo-controlled Phase 3 trials in patients undergoing open inguinal repair under general anesthesia.

In Study 1, 298 patients were enrolled. The mean age was 53.2 years (range 19 to 86) and patients were predominantly male (96%). In Study 2, 312 patients were enrolled. The mean age was 49.7 years (range 18 to 85) and patients were predominantly male (98%). In each study, three XARACOLL implants, containing 100 mg bupivacaine HCl each, were cut in half. Three halves were placed into the hernia repair site below the site of mesh placement. The muscle/fascial layer was closed and the remaining three halves were placed between the fascia/muscle closure and the skin closure. The placebo consisted of three implants without bupivacaine HCl, similarly prepared and placed. Use of low-dose lidocaine, administered topically or subcutaneously for intravenous catheter placement, or administered intravenously during the induction of general anesthesia prior to surgery and placement of XARACOLL, was reported.

Pain intensity was rated by the patients using a 0 to 10 numerical rating scale at multiple time points up to 72 hours. Immediately postoperatively, patients were allowed parenteral morphine rescue medication as needed. Once tolerating oral intake, patients received a standard acetaminophen regimen (650 mg orally three times daily) and immediate-release oral morphine (15 mg) was available as needed.

The primary outcome measure was the time-weighted sum of pain intensity from Time 0 through 24 hours (SPI24). The secondary endpoints were total use of opioid analgesia from Time 0 through 24 hours (TOpA24), time-weighted sum of pain intensity from Time 0 through 48 hours (SPI48), total use of opioid analgesia from Time 0 through 48 hours (TOpA48), time-weighted sum of pain intensity from Time 0 through 72 hours (SPI72), and total use of opioid analgesia from Time 0 through 72 hours (TOpA72).

In both Study 1 and Study 2, there was a statistically significant treatment effect for XARACOLL compared to placebo in SPI 24 and TOpA24. There was no statistically significant treatment effect for XARACOLL compared to placebo in SPI72 and TOpA72. Table 3 shows the mean sum of pain intensity over the first 24 hours after surgery.

Table 3: Mean Sum of Pain Intensity Over the First 24 Hours After Surgery (Primary Endpoint)
 | Study 1 |  | Study 2
 | XARACOLL N=197 | Placebo^1 N=101 | XARACOLL N=207 | Placebo [Placebo consisted of three collagen implants.] N=105
SPI24 [Primary endpoint] Mean (SD) | 85.9 (47.2) | 106.8 (48.2) | 88.3 (47.0) | 116.2 (44.0)
Difference [Treatment compared with placebo] 95% CI | -20.8 (-32.2, -9.4) |  | -27.8 (-38.6, -17.1)

SD=standard deviation; CI=confidence interval;
SPI (sum of pain intensity):

The proportion of patients who did not receive opioid rescue analgesia through 72 hours in the XARACOLL and placebo treatment groups was 36% and 22%, respectively, in Study 1, and 28% and 12%, respectively, in Study 2. The median time to first opioid rescue analgesia in the XARACOLL and placebo treatment groups was 11 hours and 1 hour, respectively, in Study 1, and 6 hours and 1 hour, respectively in Study 2.

16. HOW SUPPLIED/STORAGE AND HANDLING

XARACOLL (bupivacaine HCl) implant is supplied as three white to off-white sterile surgical implants (approximately 5 cm × 5 cm × 0.5 cm), each containing 100 mg bupivacaine HCl in individually sealed blister packages. A tray of three blister packages in a sterile pouch is provided in one carton. XARACOLL is available as:

- Four single-use cartons, each containing one pouch containing 3 x 100 mg implants (NDC 51715-100-04)
- Ten single-use cartons, each containing one pouch containing 3 x 100 mg implants (NDC 51715-100-10)

Storage

XARACOLL should be stored at 20°C to 25°C (68°F to 77°F), excursions permitted between 15°C and 30°C (between 59°F and 86°F). Brief exposure to temperatures up to 40°C (104°F) may be tolerated provided the mean kinetic temperature does not exceed 25°C (77°F); however, such exposure should be minimized.

Handling

Prior to surgical placement:

- Do not use if pouch or blister packaging has been compromised
- Avoid excessive handling
- Keep away from moisture
- Maintain sterility

17. PATIENT COUNSELING INFORMATION

Allergic-Type Reactions

Assess if the patient has had allergic-type reactions to amide-type local anesthetics or to other formulation ingredients [see Contraindications (4), Adverse Reactions (6)].

Methemoglobinemia

Inform patients that use of local anesthetics may cause methemoglobinemia, a serious condition that must be treated promptly. Advise patients or caregivers to seek immediate medical attention if they or someone in their care experience the following signs or symptoms: pale, gray, or blue colored skin (cyanosis); headache; rapid heart rate; shortness of breath; lightheadedness; or fatigue.

Innocoll Pharmaceuticals Limited
Athlone, Ireland N37 VW42

USA Patent Number: RE47,826 E

Sep 2020; Version 1.6

PACKAGE LABEL

NDC 51715-100-03

xaracoll®

(bupivacaine HCl) implant

100 mg per implant

Pharmacist: Please dispense as 1 pouch

For surgical implantation

Rx only

1 POUCH CONTAINING

3 x 100 mg STERILE IMPLANTS

LOT: EXP:

PACKAGE LABEL

NDC 51715-100-03

xaracoll®

(bupivacaine HCl) implant

100 mg per implant

Rx only

1 POUCH CONTAINING 3 x 100 mg STERILE IMPLANTS

Each implant contains: bupivacaine HCl 100 mg (equivalent to 88.8 mg bupivacaine)

Dosage: 3 implants equivalent to 300 mg of bupivacaine HCl

Store at 20°C to 25°C (68°F to 77°F); excursions permitted between 15°C and 30°C (between 59°F and 86°F).

Do not use if pouch or blister packaging is damaged.

Pharmacist: Please dispense as 1 pouch

For surgical implantation

innocoll

Distributed by: Innocoll Pharmaceuticals Ltd. Athlone, Ireland N37 VW42

PACKAGE LABEL

NDC 51715-100-10

xaracoll®

(bupivacaine HCl) implant

100 mg per implant

Rx only

CONTAINS 10 SINGLE-USE CARTONS, EACH CONTAINING 1 POUCH CONTAINING 3 x 100 mg STERILE IMPLANTS

Each implant contains: bupivacaine HCl 100 mg (equivalent to 88.8 mg bupivacaine)

Dosage: 3 implants equivalent to 300 mg of bupivacaine HCl

Store at 20°C to 25°C (68°F to 77°F); excursions permitted between 15°C and 30°C (between 59°F and 86°F).

Do not use if pouch or blister packaging is damaged.

Pharmacist: Please dispense as a single-use carton containing 1 pouch

For surgical implantation

Distributed by:

Innocoll Pharmaceuticals Ltd. Athlone, Ireland N37 VW42

innocoll

PACKAGE LABEL

NDC 51715-100-04

xaracoll®

(bupivacaine HCl) implant

100 mg per implant

Rx only

CONTAINS 4 SINGLE-USE CARTONS, EACH CONTAINING 1 POUCH CONTAINING 3 x 100 mg STERILE IMPLANTS

Each implant contains: bupivacaine HCl 100 mg (equivalent to 88.8 mg bupivacaine)

Dosage: 3 implants equivalent to 300 mg of bupivacaine HCl

Store at 20°C to 25°C (68°F to 77°F); excursions permitted between 15°C and 30°C (between 59°F and 86°F).

Do not use if pouch or blister packaging is damaged.

Pharmacist: Please dispense as a single-use carton containing 1 pouch

For surgical implantation

innocoll

Distributed by: Innocoll Pharmaceuticals Ltd. Athlone, Ireland N37 VW42